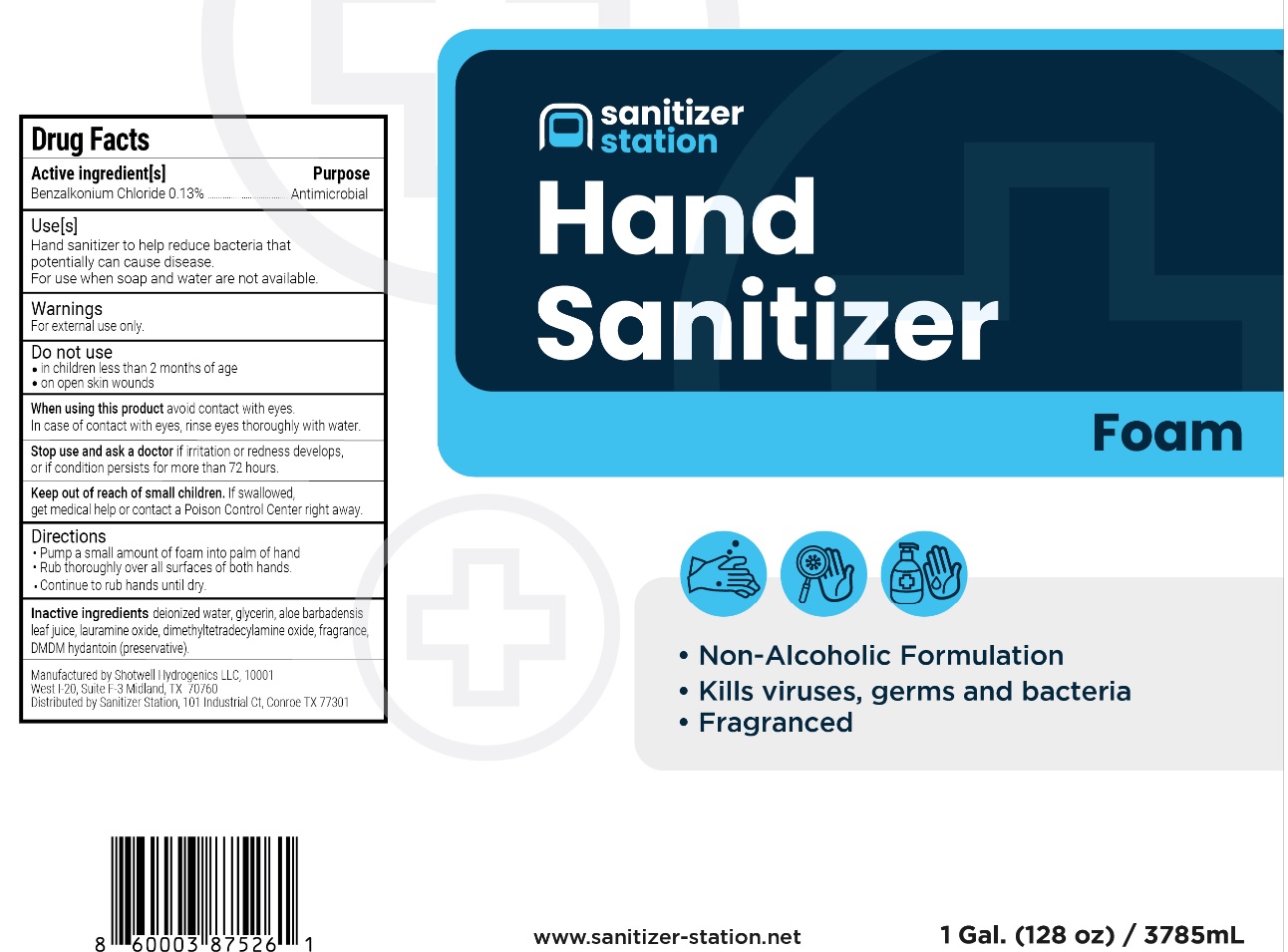 DRUG LABEL: Sanitizer Station Hand Sanitizer Foam
NDC: 82062-201 | Form: SOLUTION
Manufacturer: Pharmore Group LLC DBA Sanitizer Station
Category: otc | Type: HUMAN OTC DRUG LABEL
Date: 20210107

ACTIVE INGREDIENTS: BENZALKONIUM CHLORIDE 1.3 g/1000 mL
INACTIVE INGREDIENTS: WATER; GLYCERIN; ALOE VERA LEAF; LAURAMINE OXIDE; MYRISTAMINE OXIDE; DMDM HYDANTOIN

Sanitizer Station Hand Sanitizer Foam

Active Ingredient[s]

Benzalkonium Chloride 0.13%

Purpose

Antimicrobial

Use[s]

Hand sanitizer to help reduce bacteria that potentially can cause disease.
For use when soap and water are not available.

Warnings

For external use only.

Do not use
• in children less than 2 months of age
• on open skin wounds

When using this product avoid contact with eyes.
In case of contact with eyes, rinse eyes thoroughly with water.

Stop use and ask doctor if irritation or redness develops, or if condition persists for more than 72 hours.

Keep out of reach of children. If swallowed, get medical help or contact a Poison Control Center right away.

Directions

- Pump a small amount of foam into palm of hand.
- Rub thoroughly over all surfaces of both hands.
- Continue to rub hands until dry.

Inactive Ingredients

deionized water, glycerin, aloe barbadensis leaf juice, lauramine oxide, dimethyltetradecylamine oxide, fragrance, DMDM hydantoin (preservative).

- Non-Alcoholic Formulation
- Kills viruses, germs and bacteria
- Fragranced

www.sanitizer-station.net

Manufactured by Shotwell Hydrogenics LLC, 10001
West l-20, Suite F-3 Midland, TX 70760
Distributed by Sanitizer Station, 101 Industrial Ct, Conroe, TX, 77301